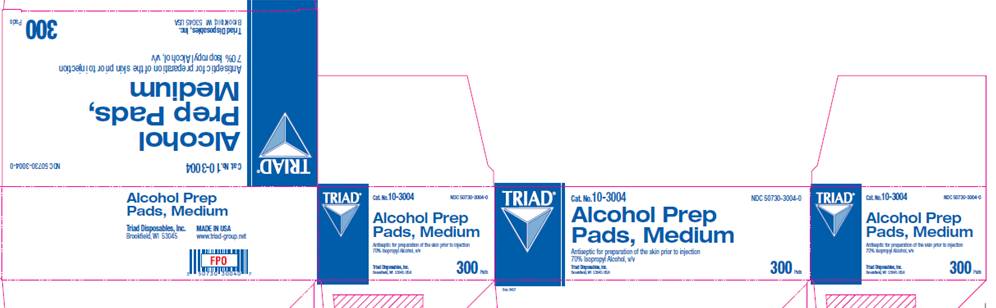 DRUG LABEL: Isopropyl alcohol
NDC: 50730-3004 | Form: SWAB
Manufacturer: H and P Industries, Inc. dba Triad Group
Category: otc | Type: HUMAN OTC DRUG LABEL
Date: 20091216

ACTIVE INGREDIENTS: Isopropyl alcohol .7 mL/1 1
INACTIVE INGREDIENTS: water

DRUG FACTS

ACTIVE INGREDIENT

Isopropyl Alcohol 70% v/v

PURPOSE

Antiseptic

USES

for preparation of the skin prior to injection

WARNINGS

- For external use only

- Flammable, keep away from fire or flame

Do not use

- with electrocautery procedures
- in the eyes

Stop use

if irritation and redness develop.

Ask a doctor

if condition persists for more than 72 hours.

KEEP OUT OF REACH OF CHILDREN

If swallowed, get medical help or contact a Poison Control Center right away.

DIRECTIONS

wipe injection site vigorously

OTHER INFORMATION

store at room temperature

INACTIVE INGREDIENT

water

PACKAGE INFORMATION

TRIAD
Cat No. 10-3004
NDC 50730-3004-0
Alcohol Prep Pads, Medium
Antiseptic for preparation of the skin prior to injection
70% Isopropyl Alcohol, v/v
300 Pads
Triad Disposables, Inc.
Brookfield, WI 53045 USA